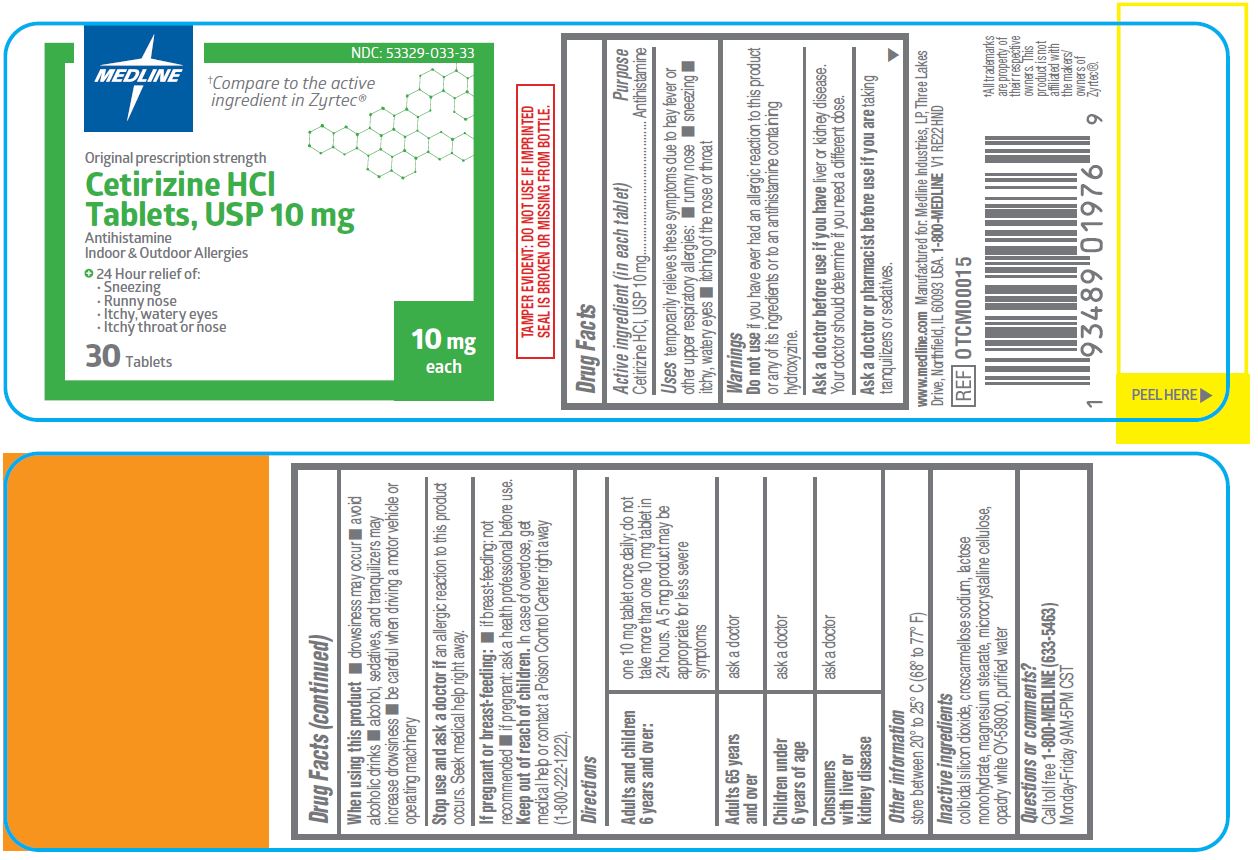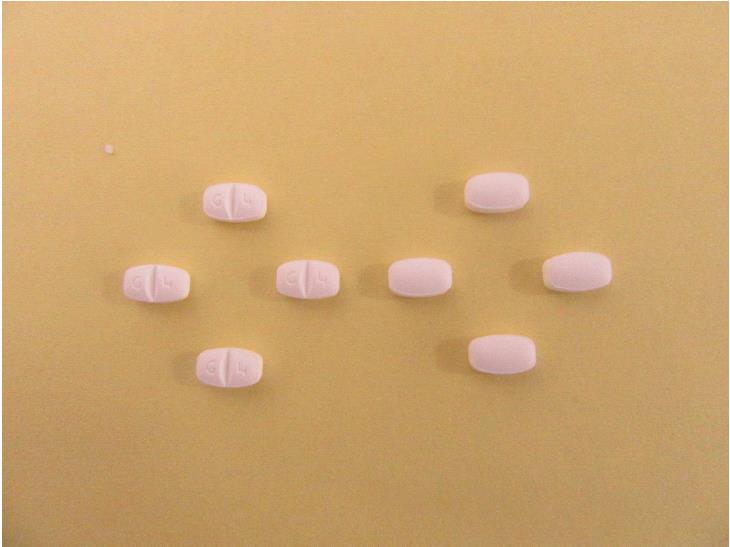 DRUG LABEL: Medline
NDC: 53329-033 | Form: TABLET
Manufacturer: Medline Industries, LP
Category: otc | Type: HUMAN OTC DRUG LABEL
Date: 20241126

ACTIVE INGREDIENTS: CETIRIZINE HYDROCHLORIDE 10 mg/1 1
INACTIVE INGREDIENTS: SILICON DIOXIDE; MAGNESIUM STEARATE; MICROCRYSTALLINE CELLULOSE; WATER; CROSCARMELLOSE SODIUM; LACTOSE MONOHYDRATE

033 Cetirizine HCl tablets

Active ingredient (in each tablet)

Cetirizine HCl, USP 10 mg

Purpose

Antihistamine

Uses

temporarily relieves these symptoms due to hay fever or other upper respiratory allergies:

- runny nose
- sneezing
- itchy, watery eyes
- itching of the nose or throat

Warnings

Do not use

if you have ever had an allergic reaction to this product or any of its ingredients or to an antihistamine containing hydroxyzine.

Ask a doctor before use if you have

liver or kidney disease. Your doctor should determine if you need a different dose.

Ask a doctor or pharmacist before use

if you are taking tranquilizers or sedatives.

When using this product

- drowsiness may occur
- avoid alcoholic drinks
- alcohol, sedatives, and tranquilizers may increase drowsiness
- be careful when driving a motor vehicle or operating machinery

Stop use and ask a doctor if

an allergic reaction to this product occurs. Seek medical help right away.

If pregnant or breast-feeding:

- if breast-feeding: not recommended
- if pregnant: ask a health professional before use.

Keep out of reach of children.

In case of overdose, get medical help or contact a Poison Control Center right away (1-800-222-1222).

Directions

adults and children 6 years and over | one 10 mg tablet once daily; do not take more than one 10 mg tablet in 24 hours. A 5 mg product may be appropriate for less severe symptoms
adults 65 years and over | ask a doctor
children under 6 years of age | ask a doctor
consumers with liver or kidney disease | ask a doctor

Other information

store between 20º -25ºC (68º -77ºF)

Inactive ingredients

colloidal silicon dioxide, croscarmellose sodium, lactose monohydrate, magnesium stearate, microcrystalline cellulose, opadry white OY-58900, purified water

Questions or comments?

Call toll free 1-800-MEDLINE (633-5463)

Monday-Friday 9AM-5PM CST

Manufacturing Information

Manufactrued for:

Medline Industries, LP

Three Lakes Drive, Northfield, IL 60093 USA

www.medline.com

1-800-MEDLINE (633-5463)

REF: OTCM00015

V1 RE22HND